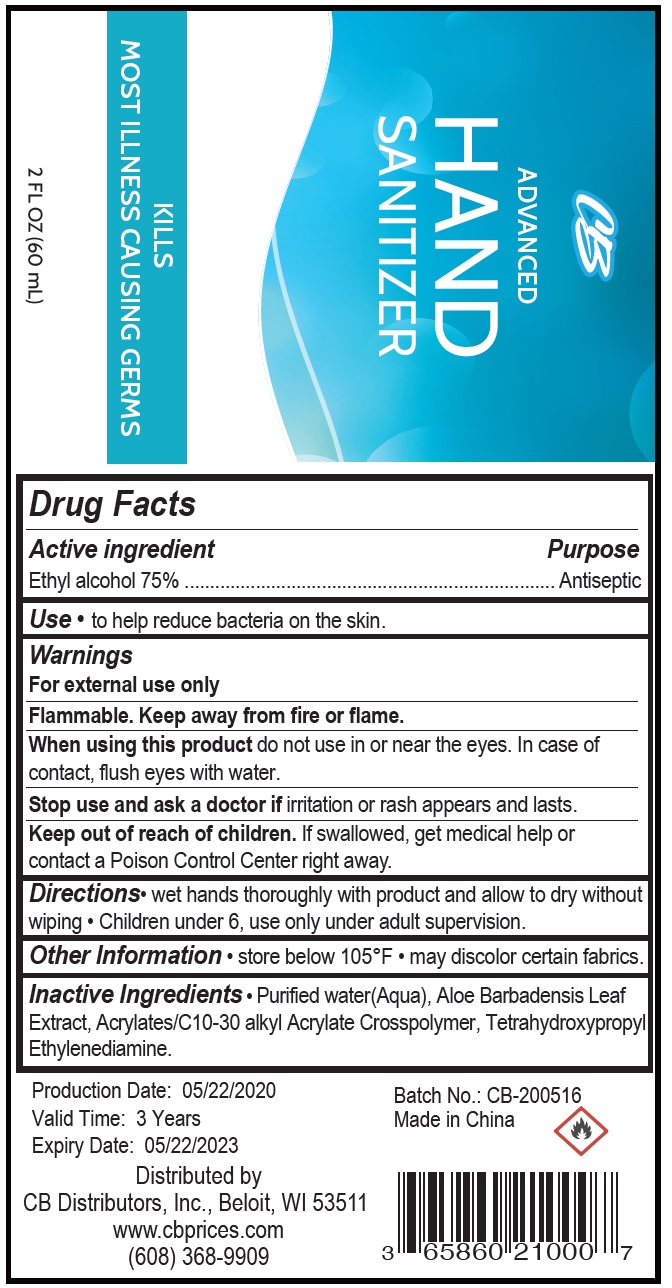 DRUG LABEL: CB Advanced Hand Sanitizer
NDC: 76813-014 | Form: GEL
Manufacturer: Cb Distributors, Inc.
Category: otc | Type: HUMAN OTC DRUG LABEL
Date: 20200611

ACTIVE INGREDIENTS: ALCOHOL 0.75 mL/1 mL
INACTIVE INGREDIENTS: WATER; ALOE VERA LEAF; CARBOMER INTERPOLYMER TYPE A (ALLYL SUCROSE CROSSLINKED); EDETOL

CB Advanced Hand Sanitizer

Active ingredient

Ethyl alcohol 75%

Purpose

Antiseptic

Use

• to help reduce bacteria on the skin.

Warnings

For external use only

Flammable. Keep away from fire or flame.

When using this product

do not use in or near the eyes. In case of contact, flush eyes with water.

Stop use and ask a doctor if

irritation or rash appears and lasts.

Keep out of reach of children.

If swallowed, get medical help or contact a Poison Control Center right away.

Directions

• wet hands thoroughly with product and allow to dry without wiping • Children under 6, use only under adult supervision.

Other Information

• store below 105°F • may discolor certain fabrics.

Inactive Ingredients

• Purified water(Aqua), Aloe Barbadensis Leaf Extract, Acrylates/C10-30 alkyl Acrylate Crosspolymer, Tetrahydroxypropyl Ethylenediamine.